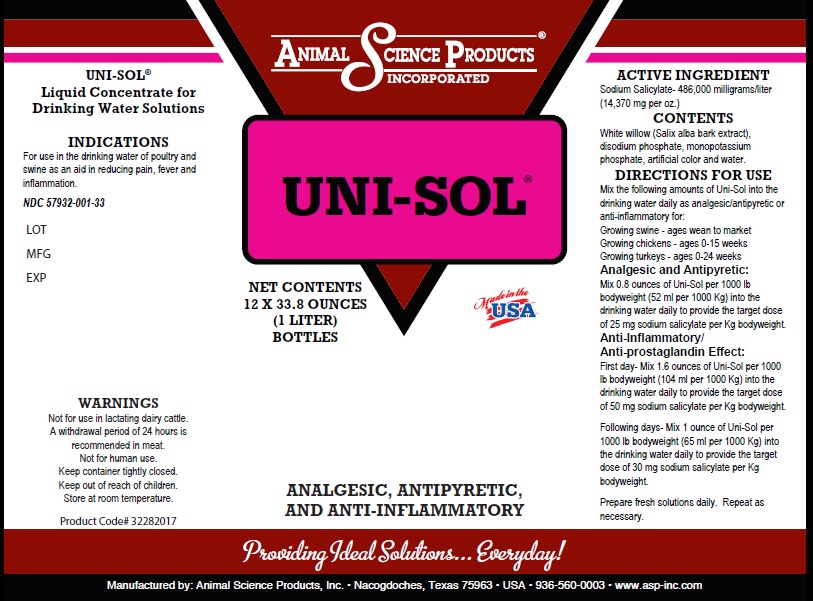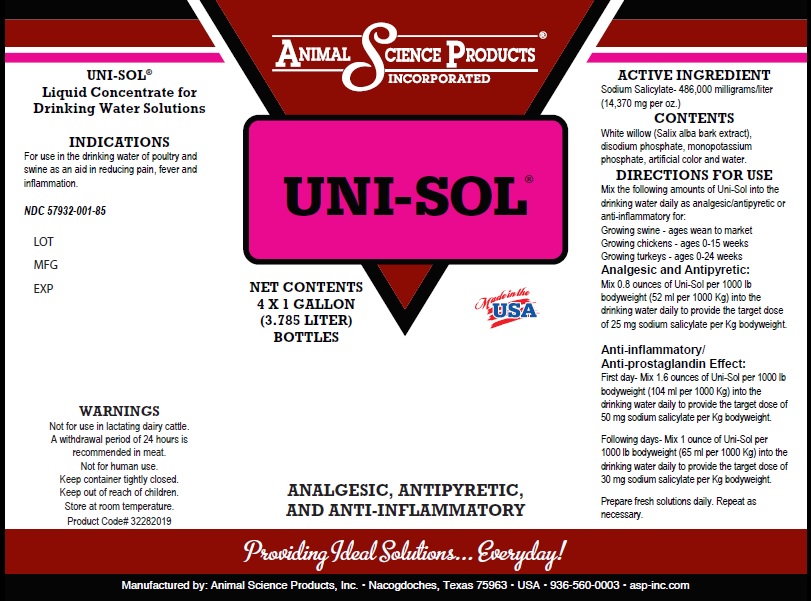 DRUG LABEL: UNI-SOL
NDC: 57932-001 | Form: SOLUTION
Manufacturer: Animal Science Products Inc
Category: animal | Type: OTC ANIMAL DRUG LABEL
Date: 20251028

ACTIVE INGREDIENTS: SODIUM SALICYLATE 486000 mg/1 L
INACTIVE INGREDIENTS: WATER

UNISOL

Ingredients

Active ingredient: Each liter contains 486,000 mg Sodium Salicylate (14,370mg per ounce)

Directions for Use

Mix the following amounts of Uni-Sol® into the drinking water daily as analgesic/antipyretic or anti-inflammatory for:
Growing swine - ages wean to market
Growing chickens - ages 0-15 week
Growing turkeys - ages 0-24 weeks
Analgesic and Antipyretic:
Mix 0.8 ounces of Uni-Sol® per 1000 lb bodyweight (52 ml per 1000 Kg) into th drinking water daily to provide the target dose
of 25 mg sodium salicylate per Kg bodyweight.
Anti-inflammatory/Anti-prostaglandin Effect:
First day- Mix 1.6 ounces of Uni-Sol® per 1000 lb bodyweight (104 ml per 1000 Kg) into the drinking water daily to provide
the target dose of 50 mg sodium salicylate per Kg bodyweight.
Following days- Mix 1 ounce of Uni-Sol® per 1000 lb bodyweight (65 ml per 1000 Kg) into the drinking water daily to
provide the target dose of 30 mg sodium salicylate per Kg bodyweight.
Prepare fresh solutions daily. Repeat as necessary.

Indications

For use in the drinking water of poultry and swine as an

PURPOSE

aid in reducing pain, fever and inflammation

Warnings

Not for use in lactating dairy cattle.
A withdrawal period of 24 hours is recommended in meat.
Not for human use.
Keep container tightly closed.
Keep out of reach of children.
Store at room temperature.

Excipients

Water and artificial color

Product Labeling

Uni-Sol

Net Contents 33.8 oz (1 Liter)

Net Contents 1 Gallon (3.785 Liter)

Analgesic, Antipyretic, and Anti-Inflammatory

Providing Ideal Solutions.. Everyday!

Manufactured by Animal Science Products, Inc - Nacogdoches, Texas 75963 - USA - 936-560-0003 - www.asp-inc.com